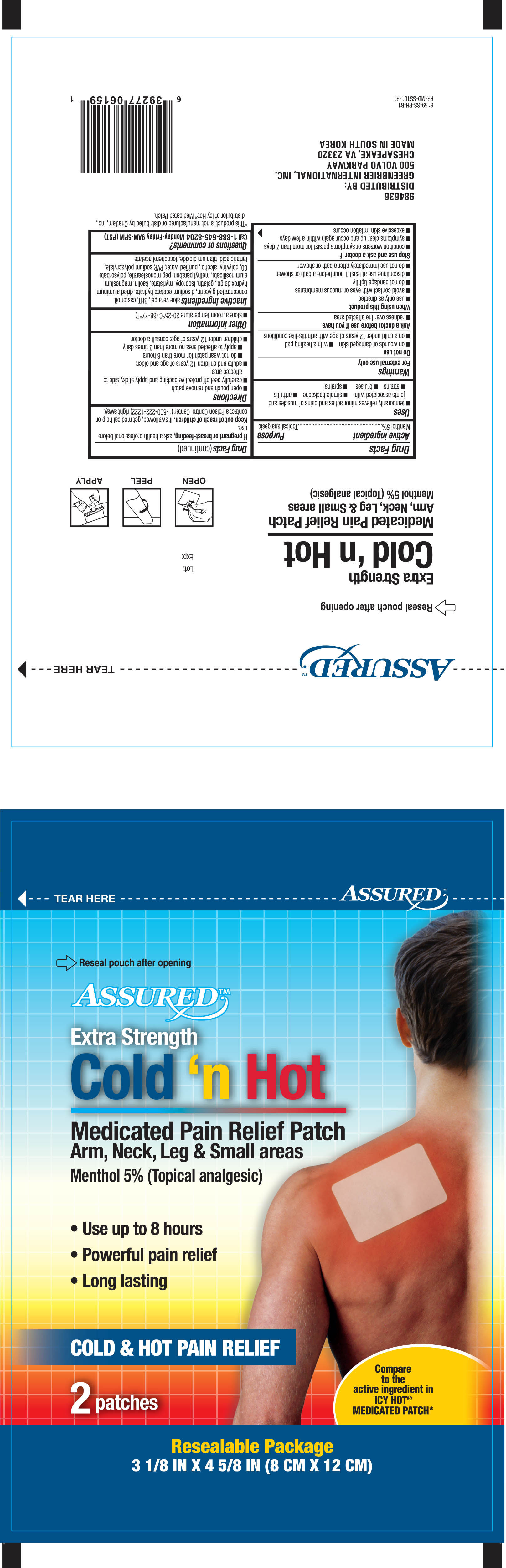 DRUG LABEL: Assured Cold N Hot Pain Relief Menthol
NDC: 33992-6159 | Form: PATCH
Manufacturer: Greenbrier International, Inc
Category: otc | Type: HUMAN OTC DRUG LABEL
Date: 20201028

ACTIVE INGREDIENTS: MENTHOL 5 mg/100 mg
INACTIVE INGREDIENTS: ALOE VERA LEAF; ALUMINUM HYDROXIDE; CASTOR OIL; EDETATE DISODIUM; GELATIN; GLYCERIN; ISOPROPYL MYRISTATE; KAOLIN; MAGNESIUM ALUMINUM SILICATE; METHYLPARABEN; POLYETHYLENE GLYCOL 1000; POLYSORBATE 80; POLYVINYL ALCOHOL; WATER; SODIUM POLYACRYLATE (8000 MW); TARTARIC ACID; TITANIUM DIOXIDE; .ALPHA.-TOCOPHEROL ACETATE; BUTYLATED HYDROXYTOLUENE

Assured Cold'n Hot Medicated Patch 2ct 6159, 2020

Active Ingredient Purpose

Menthol 5%--------------------------------------------------------- Topical analgestic

Uses

Temporarily relieves minor pains associated with:

- arthritis
- simple backache
- bursitis
- tendonitis
- muscle strains
- muscle cramps

Warnings

For external use only

Do not use

- on wounds or damaged skin
- with a heating pad
- on a child under 12 years of age with arthritis-like conditions

Ask a doctor before use if you have

- redness over the affected area

When using this product

- use as only directed
- avoid contact with eyes and mucous membranes
- do not bandage tightly
- discontinue use at least 1 hour before a bath or shower
- do not use immediately after a bath or shower

Stop use and ask a doctor if

- condition worsens or symptoms persist more than 7 days
- symptoms clear up and occur again within a few days
- excessive skin irritation occurs

PREGNANCY OR BREAST FEEDING

If pregnant or breast-feeding, ask a health professional before use.

Keep out of reach of children. If swallowed, get medical help or contact a Poison Control Center (1-800-222-1222) right away.

Directions

- open pouch and remove patch
- carefully peel off protective packing and apply sticky side to affected area
- adults and children 12 years of age and older:
- do not wear patch for more than 8 hours
- apply to affected area no more than 3 times daily
- children under 12 years of age: consult a doctor

Other information

- store at room temperature 20-25°C (68-77°F)

Inactive ingredients

aloe vera, aluminum hydroxide, BHT, castor oil, concentrated glycerin, disodium edetate hydrate, dried aluminum hydroxide gel, gelatin, isopropyl myristate, kaolin, magnesium aluminosilicate, methyl paraben, peg monostearate, polysorbate 80, polyvinyl alcohol, purified water, PVP, sodium polyacrylate, tartaric dioxide, tocopherol acetate

DOSAGE AND ADMINISTRATION

DISTRIBUTED BY

GREENBRIER INTERNATIONAL, INC.

500 VOLVO PARKWAY

CHESAPEAKE, VA 23320

MADE IN KOREA